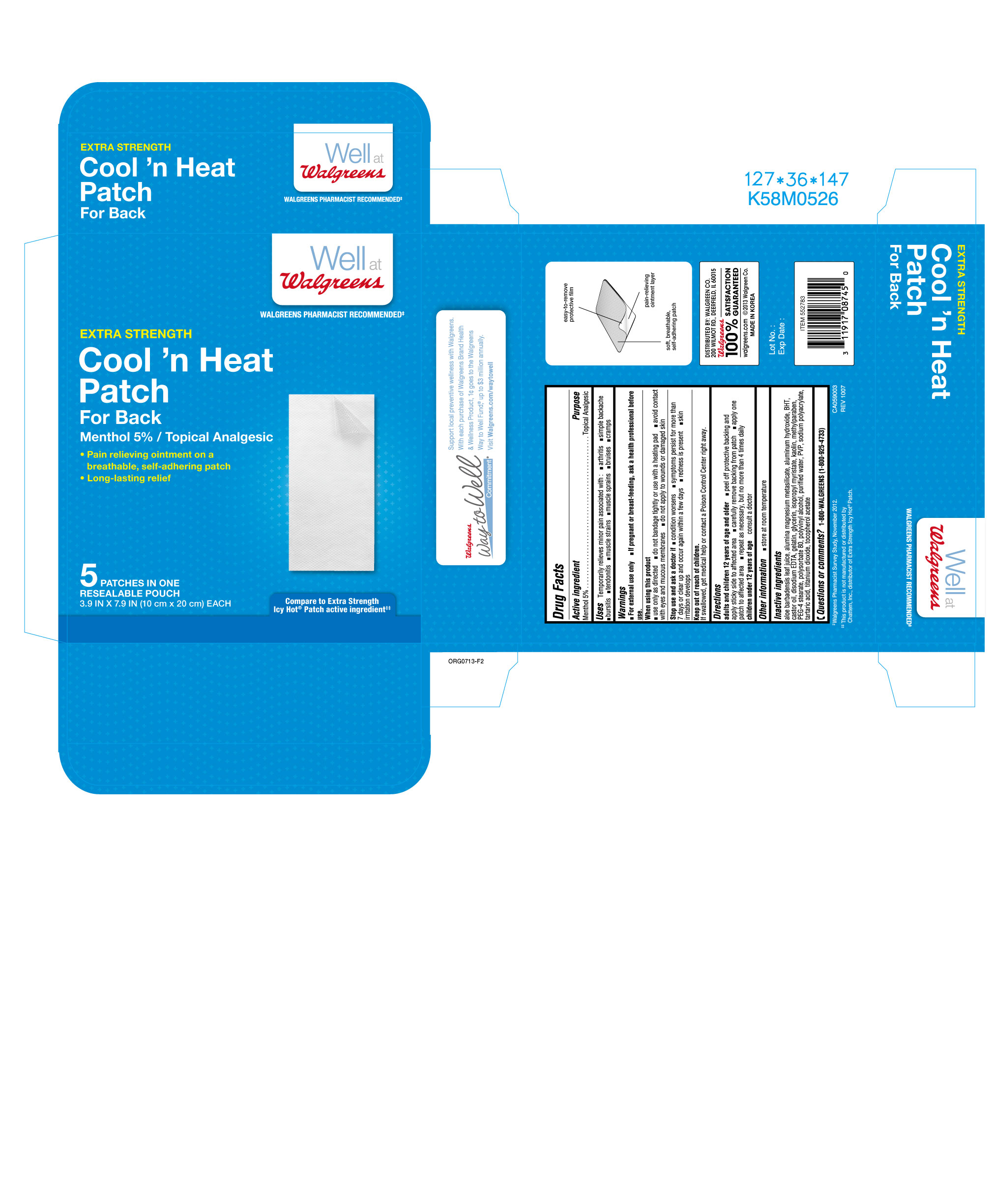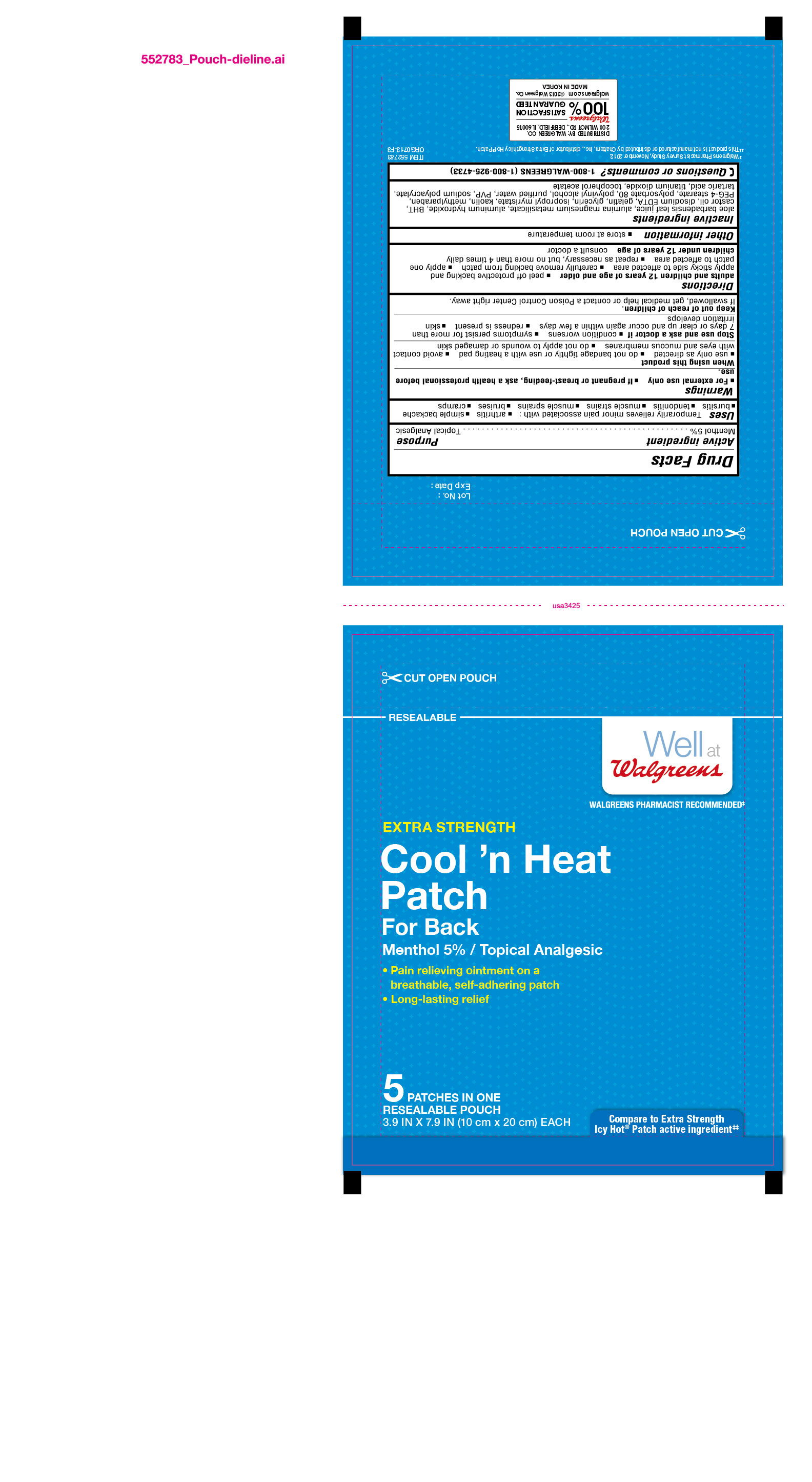 DRUG LABEL: Cool n Heat Patch for Back
NDC: 0363-0152 | Form: PATCH
Manufacturer: Walgreen Co.
Category: otc | Type: HUMAN OTC DRUG LABEL
Date: 20131015

ACTIVE INGREDIENTS: Menthol .05 mg/1 g
INACTIVE INGREDIENTS: Aloe Vera Leaf; Aluminum Hydroxide; Edetate Disodium; Gelatin; Kaolin; Methylparaben; Glycerin; Titanium Dioxide; Isopropyl Myristate; Water; PEG-4 Stearate; Polyvinyl Alcohol; Polysorbate 80; Alpha-Tocopherol Acetate; Silodrate; Castor Oil; Tartaric Acid; Butylated Hydroxytoluene

Menthol 5% (Topical Analgesic)

Active Ingredient

Menthol 5%

Purpose

Topical Analgesic

Uses

Temporarily relieves minor pain associated with:

- arthritis
- simple backache
- bursitis
- tendonitis
- muscle strains
- muscle sprains
- bruises
- cramps

Warnings

- For external use only
- If pregnant or breast-feeding, ask a health professional before use.

When using this product

- use only as directed
- do not bandage tightly or use with a heating pad
- avoid contact with eyes and mucous membranes
- do not apply to wounds or damaged skin

Stop use and ask a doctor if

- conditions worsens
- symptoms persist for more than 7 days or clear up and occur again within a few days
- redness is present
- skin irritation develops

Keep out of reach of children.

If swallowed, get medical help or contact a Poison Control Center right away.

Directions

adults and children 12 years of age and older

- peel off protective backing and apply sticky side to affected area
- carefully remove backing from patch
- apply one patch to affected area
- repeat as necessary, but no more than 4 times daily

Children under 12 years of age consult a doctor

Other information

- store at room temperature

Inactive ingredients

aloe barbadensis leaf juice, alumina magnesium metasilicate, aluminum hydroxide, BHT, castor oil, disodium EDTA, gelatin, glycerin, isopropyl myristate, kaolin, methylparaben, PEG-4 stearate, polysorbate 80, polyvinyl alcohol, purified water, PVP, sodium polyacrylate, tartaric acid, titanium dioxide, tocopherol acetate

Questions or comments?

1-800-WALGREENS (1-800-925-4733)